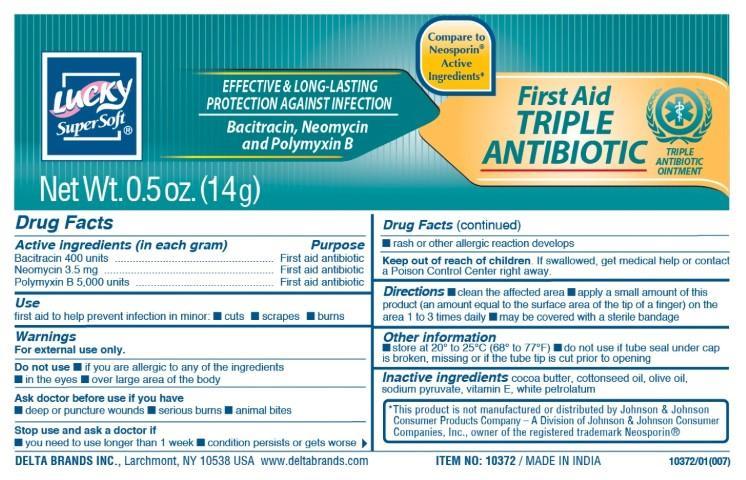 DRUG LABEL: Lucky SuperSoft
NDC: 47046-175 | Form: OINTMENT
Manufacturer: Anicare Pharmaceuticals pvt. Ltd.
Category: otc | Type: HUMAN OTC DRUG LABEL
Date: 20221122

ACTIVE INGREDIENTS: BACITRACIN 400 [USP'U]/1 g; NEOMYCIN SULFATE 3.5 mg/1 g; POLYMYXIN B SULFATE 5000 [USP'U]/1 g
INACTIVE INGREDIENTS: COCOA BUTTER; COTTONSEED OIL; OLIVE OIL; SODIUM PYRUVATE; ALPHA-TOCOPHEROL; PETROLATUM

Triple Anitibiotic

Active ingredients

Bacitracin 400 units

Neomycin 3.5 mg

Polymyxin B 5000 units

Purpose

First aid antibiotic

First aid antibiotic

First aid antibiotic

Use

first aid to help prevent infection in minor: ■ cuts ■ scrapes ■ burns

Warnings

For external use only

Do not use

■ if you are allergic to any of the ingredients ■ in the eyes ■ over large areas of the body

Ask a doctor before use if you have

■ deep or puncture wounds ■ serious burns ■ animal bites

Stop use and consult a doctor if

■ you need to use longer than 1 week ■ condition persists or gets worse ■ rash or other allergic reaction develops

Keep out of reach of children

if swallowed, get medical help or contact a Poison Control Center right away.

Directions

■ clean the affected area ■ apply a small amount of this product (an amount equal to the surface area of the tip of a finger) on the area 1 to 3 times daily ■ may be covered with a sterile bandage

Other information

■ store at room temperature 20 to 25C (68 to 77F) ■ do not use if tube seal under cap is broken, missing or if the tube tip is cut prior to opening

Inactive ingredients

cocoa butter, cottonseed oil, olive oil, sodium pyruvate, vitamin E, white petrolatum